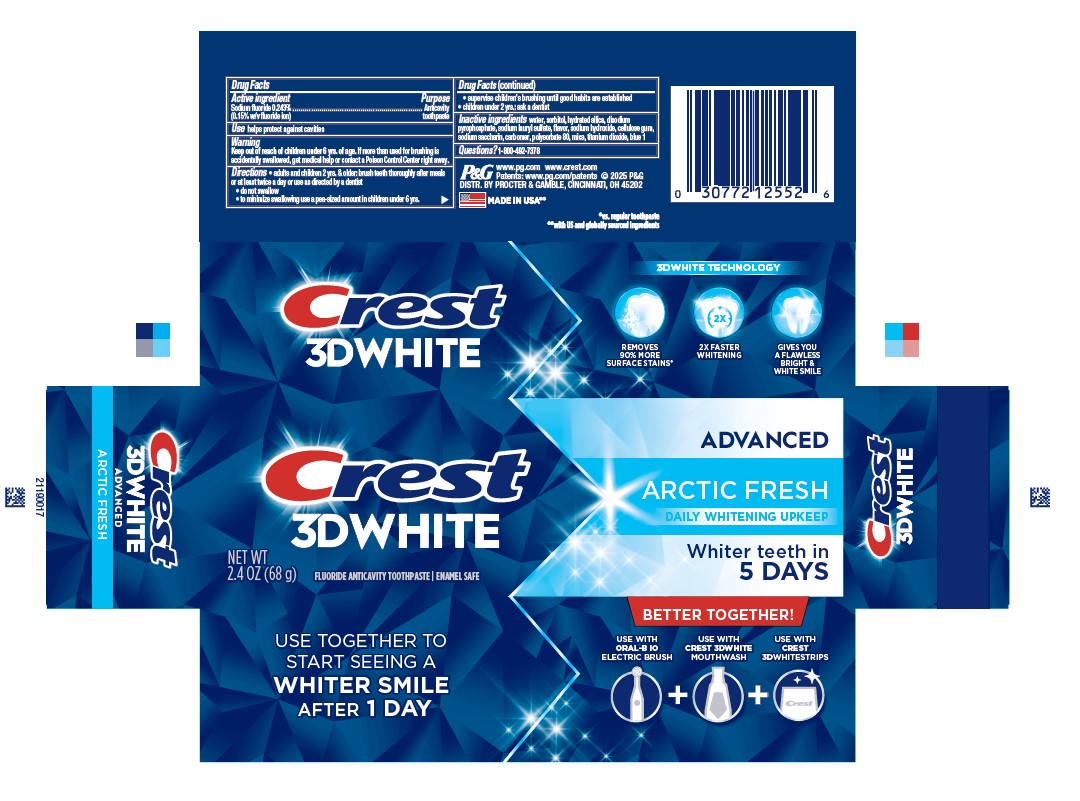 DRUG LABEL: Crest 3D White
NDC: 37000-875 | Form: PASTE, DENTIFRICE
Manufacturer: The Procter & Gamble Manufacturing Company
Category: otc | Type: HUMAN OTC DRUG LABEL
Date: 20251211

ACTIVE INGREDIENTS: SODIUM FLUORIDE 1.5 mg/1 g
INACTIVE INGREDIENTS: POLYSORBATE 80; WATER; SORBITOL; HYDRATED SILICA; SODIUM ACID PYROPHOSPHATE; SODIUM LAURYL SULFATE; SODIUM HYDROXIDE; SACCHARIN SODIUM; CARBOXYPOLYMETHYLENE; MICA; TITANIUM DIOXIDE; FD&C BLUE NO. 1; CELLULOSE GUM

Crest® 3D White™ Advanced
Arctic Fresh

Drug Facts

Active ingredient

Sodium fluoride 0.243% (0.15% w/v fluoride ion)

Purpose

Anticavity toothpaste

Use

helps protect against cavities

Warning

Keep out of reach of children under 6 yrs. of age. If more than used for brushing is accidentally swallowed, get medical help or contact a Poison Control Center right away.

Directions

- adults and children 2 yrs. & older: brush teeth thoroughly after meals or at least twice a day or use as directed by a dentist
  - do not swallow
  - to minimize swallowing use a pea-sized amount in children under 6
  - supervise children's brushing until good habits are established
- children under 2 yrs.: ask a dentist

Inactive ingredients

water, sorbitol, hydrated silica, disodium
pyrophosphate, sodium lauryl sulfate, flavor, sodium hydroxide, cellulose gum,
sodium saccharin, carbomer, polysorbate 80, mica, titanium dioxide, blue 1

Questions?

1-800-492-7378

DISTR. BY PROCTER & GAMBLE,
CINCINNATI, OH 45202

PRINCIPAL DISPLAY PANEL - 68 g Tube Carton

CREST 3D WHITE

ADVANCED

ARCTIC FRESH

DAILY WHITENING UPKEEP

WHITER TEETH IN

5 DAYS

NET WT 2.5 OZ (68g)

fluoride anticavity toothpaste

enamel safe